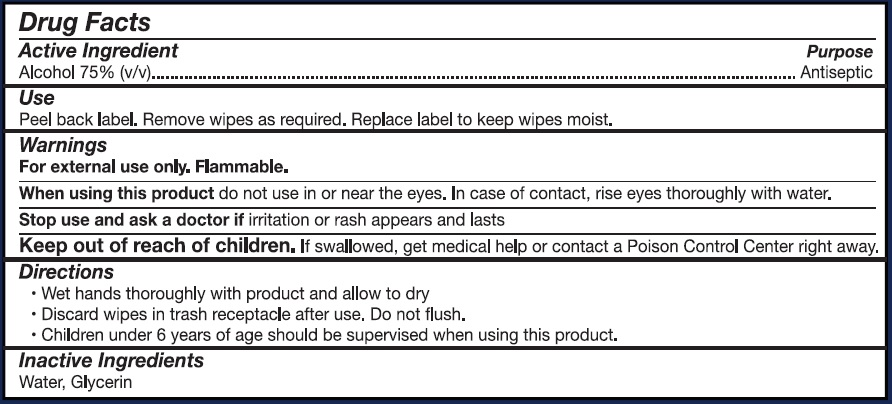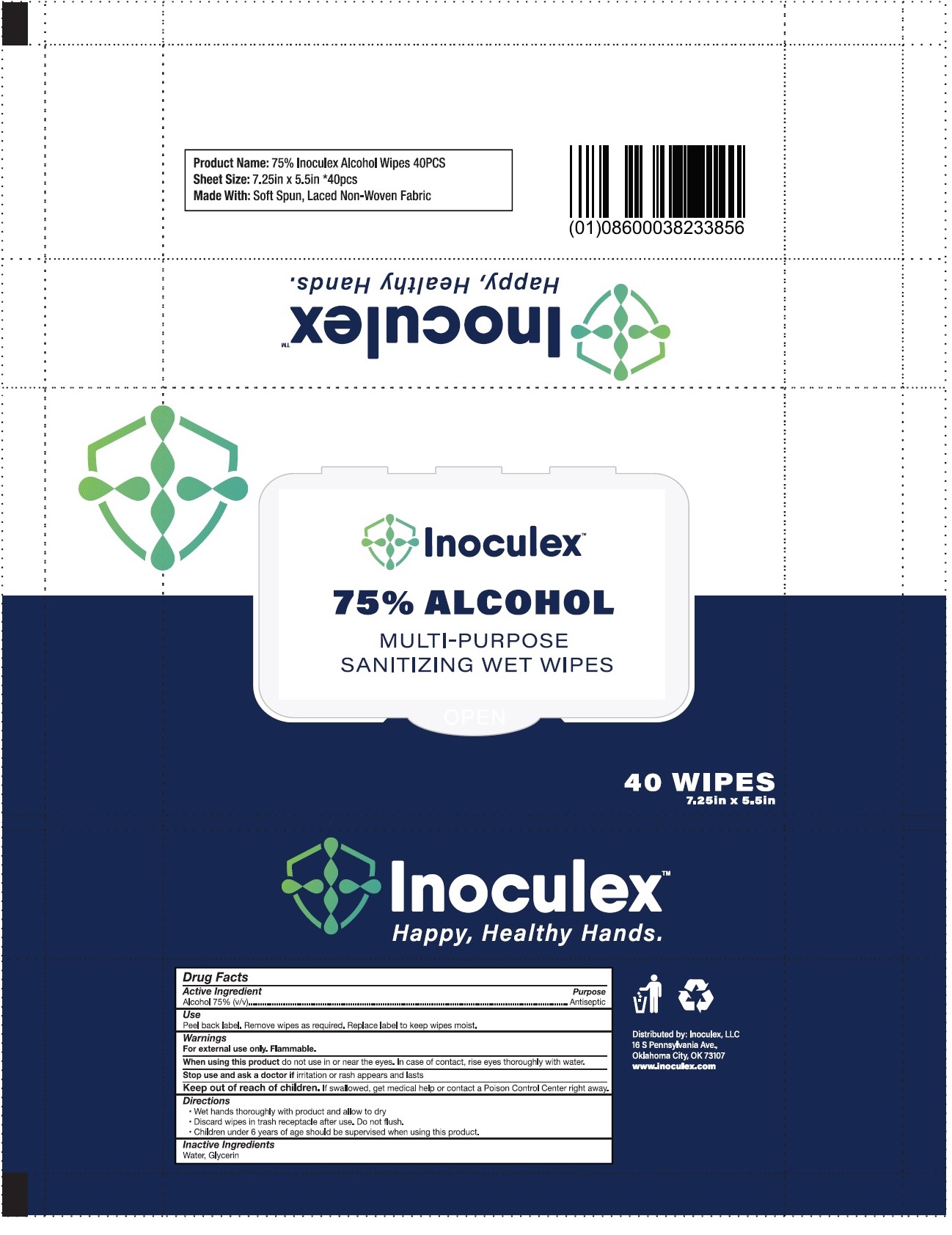 DRUG LABEL: Inoculex MULTI-PURPOSE SANITIZING WET WIPES
NDC: 77017-016 | Form: CLOTH
Manufacturer: Private Label Supplements
Category: otc | Type: HUMAN OTC DRUG LABEL
Date: 20200626

ACTIVE INGREDIENTS: ALCOHOL 75 mL/100 mL
INACTIVE INGREDIENTS: WATER; GLYCERIN

InoculexTM MULTI-PURPOSE SANITIZING WET WIPES

Active Ingredient

Alcohol 75% (v/v)

Purpose

Antiseptic

Use

Peel back label. Remove wipes as required. Replace label to keep wipes moist.

Warnings

For external use only. Flammable.

When using this product do not use in or near the eyes. In case of contact, rinse eyes thoroughly with water.

Stop use and ask a doctor if irritation or rash appears and lasts

Keep out of reach of children. If swallowed, get medical help or contact a Poison Control Center right away.

Directions

- Wet hands thoroughly with product and allow to dry
- Discard wipes in trash receptacle after use. Do not flush.
- Children under 6 years of age should be supervised when using this product.

Inactive Ingredients

Water, Glycerin

Happy, Healthy Hands.

Product Name: 75% Inoculex Alcohol Wipes 40PCS

Sheet Size: 7.25in x 5.5in *40pcs

Made with: Soft Spun, Laced Non-Woven Fabric

Distributed by: Inoculex, LLC

16 S Pennsylvania Ave.,

Oklahoma City, OK 73107

www.inoculex.com